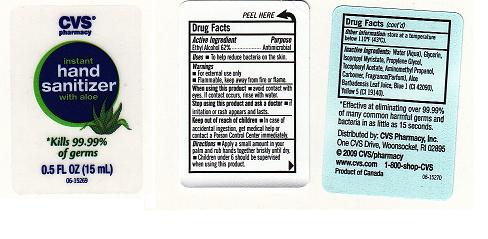 DRUG LABEL:  INSTANT HAND SANITIZER 
NDC: 59779-223 | Form: GEL
Manufacturer: CVS PHARMACY
Category: otc | Type: HUMAN OTC DRUG LABEL
Date: 20110318

ACTIVE INGREDIENTS: ALCOHOL 62 mL/100 mL
INACTIVE INGREDIENTS: WATER; GLYCERIN; ISOPROPYL MYRISTATE; PROPYLENE GLYCOL; .ALPHA.-TOCOPHEROL ACETATE, D-; AMINOMETHYLPROPANOL; CARBOMER 934; ALOE VERA LEAF; FD&C BLUE NO. 1; FD&C YELLOW NO. 5

DRUG FACTS

ACTIVE INGREDIENT

ETHYL ALCOHOL 62 PERCENT

PURPOSE

ANTIMICROBIAL

USES

TO HELP REDUCE BACTERIA ON THE SKIN.

WARNINGS

FOR EXTERNAL USE ONLY. FLAMMABLE, KEEP AWAY FROM FIRE OR FLAME.

WHEN USING THIS PRODUCT

AVOID CONTACT WITH EYES.IF CONTACT OCCURS, RINSE EYES THOROUGHLY WITH WATER.

STOP USING THIS PRODUCT AND ASK DOCTOR IF

IRRITATION OR RASH DEVELOPS AND LASTS.

KEEP OUT OF REACH OF CHILDREN

IN CASE OF ACCIDENTAL INGESTION, GET MEDICAL HELP OR CONTACT A POISON CONTROL CENTER IMMEDIATELY.

DIRECTIONS

APPLY SMALL AMOUNT IN YOUR PALM AND RUB HANDS TOGETHER BRISKLY UNTIL DRY. CHILDREN UNDER 6 SHOULD BE SUPERVISED WHEN USING THIS PRODUCT.

OTHER INFORMATION

DO NOT STORE ABOVE 110^0F (43^0C). MAY DISCOLOR CERTAIN FABRICS OR SURFACES.

INACTIVE INGREDIENTS

WATER, GLYCERIN, ISOPROPYL MYRISTATE, PROPYLENE GLYCOL, TOCOPHERYL ACETATE, AMINOMETHYL PROPANOL, CARBOMER,

FRAGRANCE, ALOE BARBADENSIS LEAF JUICE, BLUE 1 (CI 42090), YELLOW 5 (CI 19140).